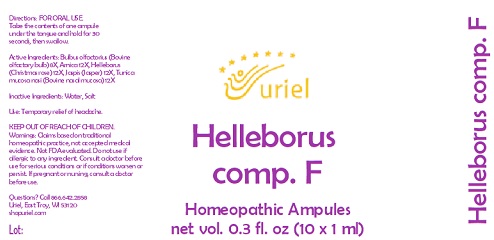 DRUG LABEL: Helleborus comp. F
NDC: 48951-5130 | Form: LIQUID
Manufacturer: Uriel Pharmacy, Inc.
Category: homeopathic | Type: HUMAN OTC DRUG LABEL
Date: 20230926

ACTIVE INGREDIENTS: SILICON DIOXIDE 12 [hp_X]/1 mL; BOS TAURUS OLFACTORY BULB 8 [hp_X]/1 mL; HELLEBORUS NIGER ROOT 12 [hp_X]/1 mL; ARNICA MONTANA 12 [hp_X]/1 mL; BOS TAURUS NASAL MUCOSA 12 [hp_X]/1 mL
INACTIVE INGREDIENTS: WATER; SODIUM CHLORIDE

Helleborus comp. F

INDICATIONS AND USAGE

Directions: FOR ORAL USE.

DOSAGE AND ADMINISTRATION

Take the contents of one ampule under the tongue and hold for 30 seconds, then swallow.

ACTIVE INGREDIENT

Active Ingredients: Bulbus olfactorius (Bovine olfactory bulb) 8X, Arnica 12X, Helleborus (Christmas rose) 12X, Jaspis (Jasper) 12X, Tunica mucosa nasi (Bovine nasal mucosa) 12X

Inactive Ingredients: Water, Salt

PURPOSE

Use: Temporary relief of headache.

KEEP OUT OF REACH OF CHILDREN.

WARNINGS

Warnings: Claims based on traditional homeopathic practice, not accepted medical evidence. Not FDA evaluated.
Do not use if allergic to any ingredient. Consult a doctor before use for serious conditions or if conditions worsen or persist.
If pregnant or nursing, consult a doctor before use.

Questions? Call 866.642.2858
Uriel, East Troy, WI 53120
shopuriel.com Lot: